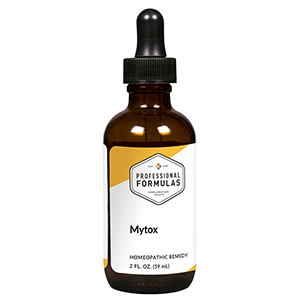 DRUG LABEL: Mytox
NDC: 63083-6021 | Form: LIQUID
Manufacturer: Professional Complementary Health Formulas
Category: homeopathic | Type: HUMAN OTC DRUG LABEL
Date: 20190815

ACTIVE INGREDIENTS: SODIUM BORATE 4 [hp_X]/59 mL; COLCHICUM AUTUMNALE BULB 4 [hp_X]/59 mL; AMANITA MUSCARIA FRUITING BODY 6 [hp_X]/59 mL; ARSENIC TRIOXIDE 6 [hp_X]/59 mL; DROSERA ROTUNDIFOLIA WHOLE 6 [hp_X]/59 mL; BUFO BUFO CUTANEOUS GLAND 8 [hp_X]/59 mL; UBIDECARENONE 12 [hp_X]/59 mL
INACTIVE INGREDIENTS: ALCOHOL; WATER

X21

ACTIVE INGREDIENTS

Borax 4X
Colchicum autumnale 4X
Agaricus muscarius 6X
Arsenicum album 6X
Drosera rotundifolia 6X
Bufo rana 8X
Coenzyme Q10 12X

QUESTIONS

Professional Formulas

PO Box 2034 Lake Oswego, OR 97035

INDICATIONS

For the temporary relief of red or itchy skin, cough, joint or muscle pain or stiffness, shortness of breath, sneezing, occasional headache, dizziness, or fatigue.*

PURPOSE

*Claims based on traditional homeopathic practice, not accepted medical evidence. Not FDA evaluated.

WARNINGS

Persistent symptoms may be a sign of a serious condition. If symptoms persist or are accompanied by a fever, rash, or persistent headache, consult a doctor. Keep out of the reach of children. In case of overdose, get medical help or contact a poison control center right away. If pregnant or breastfeeding, ask a healthcare professional before use.

Keep out of the reach of children.

PREGNANCY OR BREAST FEEDING

If pregnant or breastfeeding, ask a healthcare professional before use.

DIRECTIONS

Place drops under tongue 30 minutes before/after meals. Adults and children 12 years and over: Take 10 drops up to 3 times per day. Consult a physician for use in children under 12 years of age.

OTHER INFORMATION

Tamper resistant. If seal is broken, do not use. After opening, close container tightly and store at room temperature away from heat.

INACTIVE INGREDIENTS

20% ethanol, purified water.

LABEL

Est 1985

Professional Formulas

Complementary Health

Mytox

Homeopathic Remedy

2 FL. OZ. (59 mL)